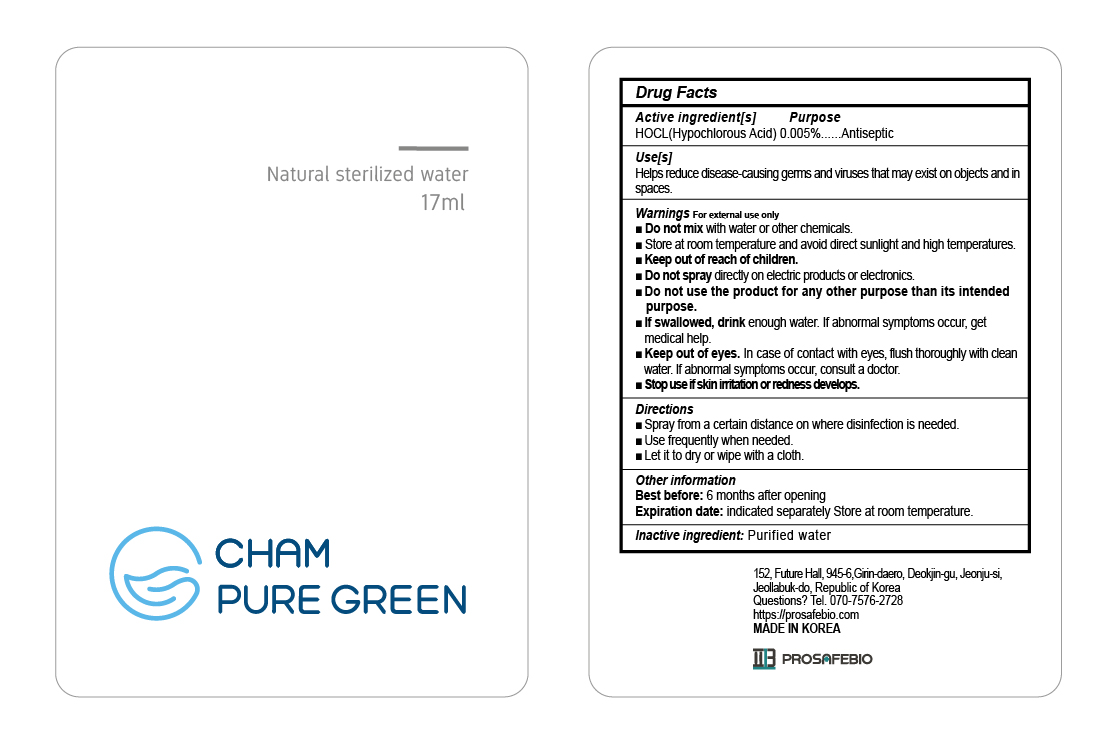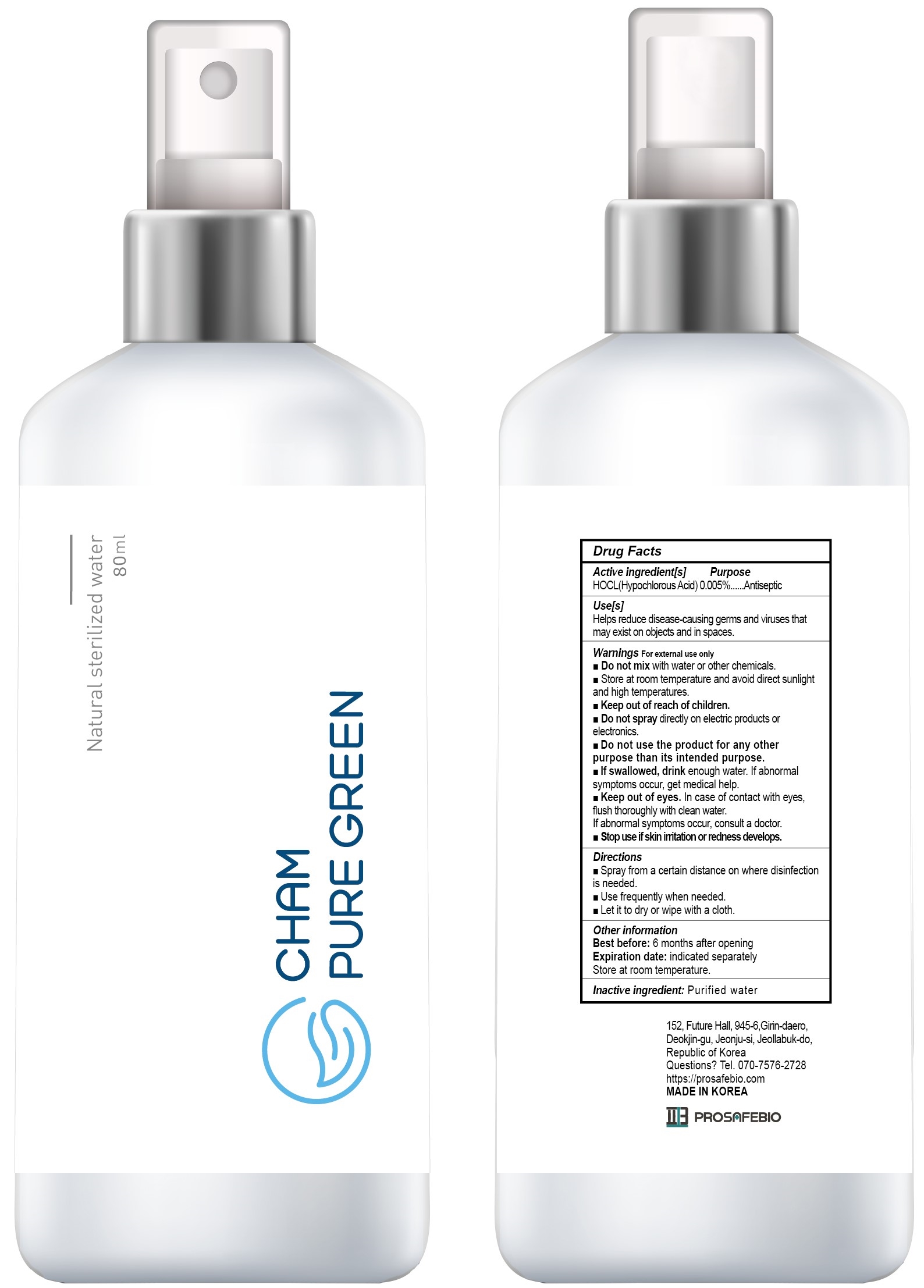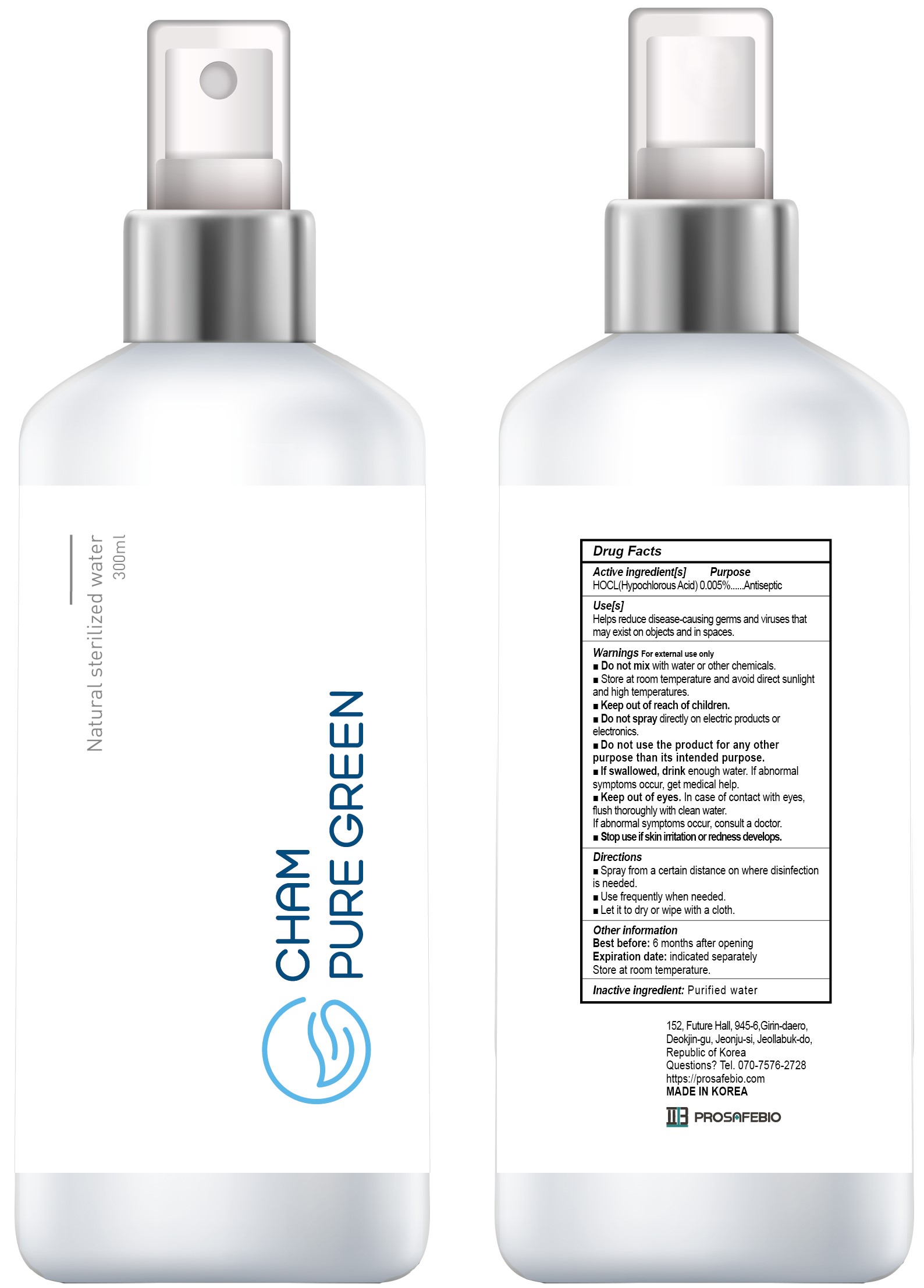 DRUG LABEL: Champuregreen
NDC: 81745-501 | Form: LIQUID
Manufacturer: PROSAFEBIO
Category: otc | Type: HUMAN OTC DRUG LABEL
Date: 20221020

ACTIVE INGREDIENTS: HYPOCHLOROUS ACID 0.005 mg/100 mL
INACTIVE INGREDIENTS: WATER

81745-501 Champuregreen

Active ingredient[s]

HOCL(Hypochlorous acid) 0.005%

Purpose

Antiseptic

Use[s]

Helps reduce disease-causing germs and viruses that may exist on objects and in spaces.

Warnings

For external use only

Do not use

- Do not mix with water or other chemicals.
- Do not spray directly on electric products or electronics.
- Do not use the product for any other purpose than its intended purpose.

Keep out of reach of children

Stop use

- If swallowed, drink enough water. If abnormal symptoms occur, get medical help.
- Keep out of eyes. In case of contact with eyes, flush thoroughly with clean water. If abnormal symptoms occur, consult a doctor.
- Stop use if skin irritation or redness develops.

Directions

- Spray from a certain distance on where disinfection is needed.
- Use frequently when needed.
- Let it to dry or wipe with a cloth.

Other information

Best before : 6 months after opening

Expiration date : indicated separately

Store at room temperature and avoid direct sunlight and high temperatures.

Inactive ingredient

Purified Water